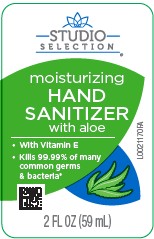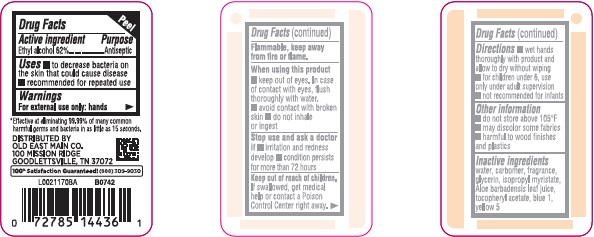 DRUG LABEL: Alcohol
NDC: 55910-889 | Form: LIQUID
Manufacturer: Old East Main Co.
Category: otc | Type: HUMAN OTC DRUG LABEL
Date: 20260302

ACTIVE INGREDIENTS: ALCOHOL 62 mL/100 mL
INACTIVE INGREDIENTS: WATER; CARBOMER INTERPOLYMER TYPE A (ALLYL SUCROSE CROSSLINKED); GLYCERIN; ISOPROPYL MYRISTATE; ALOE; TOCOPHEROL; FD&C BLUE NO. 1; FD&C YELLOW NO. 5

Studio Selection 826.000/826AA rev 1
Moisturizing Hand Sanitizer with Aloe

Active ingredient

Ethyl Alcohol 62%

Purpose

Antiseptic

Uses

- to decrease bacteria on the skin that could cause disease
- recommended for repeated use

Warnings

For external use only: hands

Flammable, keep away from fire or flame.

When using this product

- keep out of eyes. In case of contact with eyues, flush thoroughly with water.
- avoid contact with broken skin
- do not inhale of ingest

Stop use and ask a doctor if

- irritation and redness develop
- condition persists for more than 72 hours

Keep out of reach of children.

If swallowed, get medical help or contact a Poison Control Center right away.

Directions

- wet hands thoroughly with product and allow to dry without wiping
- for children under 6, use only under adult supervision
- not recommended for infants

Other information

- do not store above 105° F
- may discolor some fabrics
- harmful to wood finishes and plastic

Inactive ingredients

water, carbomer, fragrance, glycerin, isopropyl myristate, Aloe barbadensis leaf juice, tocopheryl acetate, blue 1, yellow 5

Claim

*Effective at elimnating 99.99% of many common harmful germs and bacteria in as little as 15 seconds.

ADVERSE REACTION

DISTRIBUTED BY

OLD EAST MAIN CO,

100 MISSION RIDGE

GOODLETTSVILLE, TN 37072

100% Satisfaction Guaranteed! (888)309-9030

Principal display panel

STUDIO SELECTION®

moisturizing

HAND SANITIZER with aloe

- with Vitamin E
- Kills 99.99% of many common germs & bacteria*

2 FL OZ (59 mL)